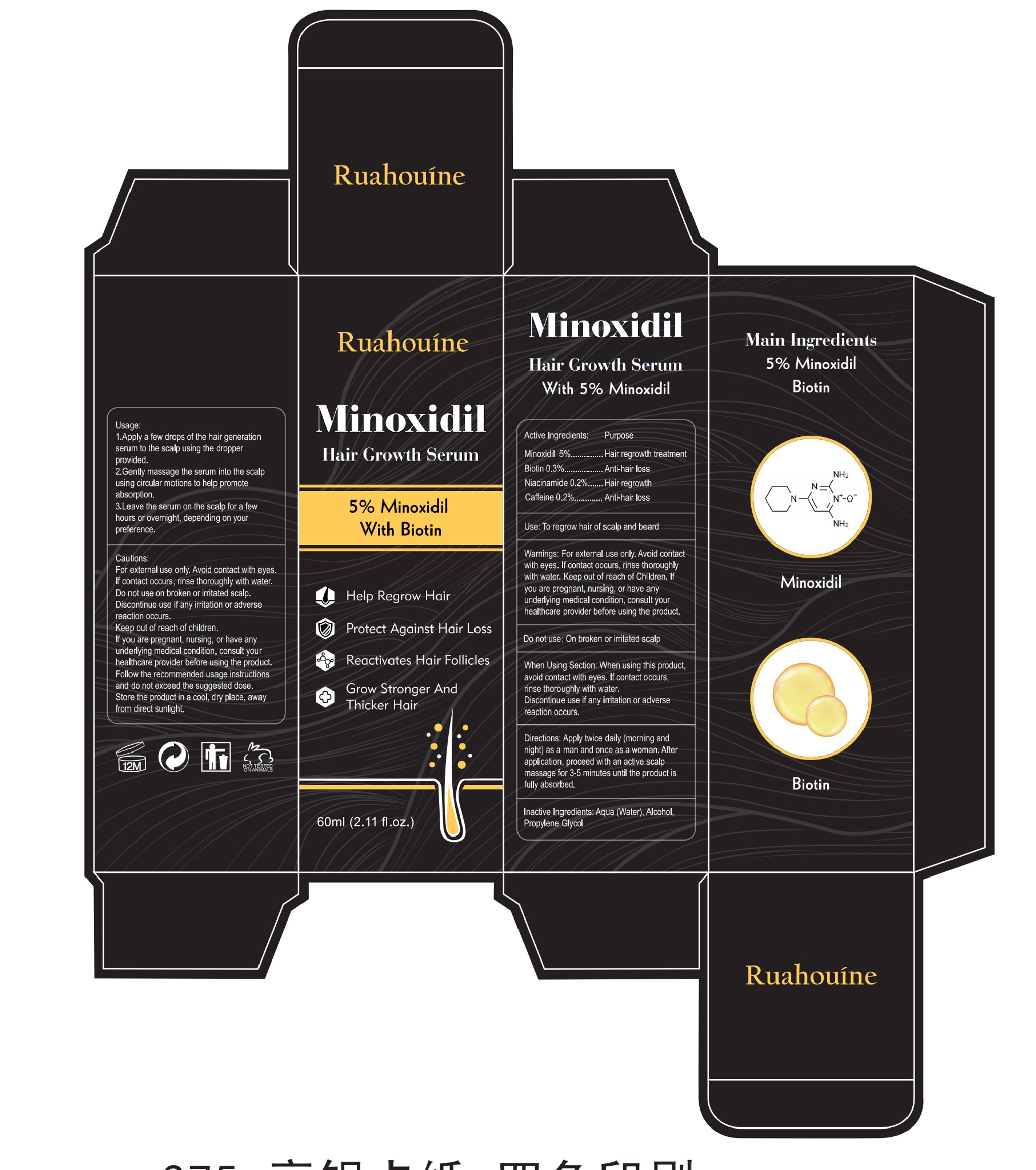 DRUG LABEL: 5%Minoxidil Hair Growth Serum
NDC: 84355-003 | Form: LIQUID
Manufacturer: Guangzhou Binsi Clothing Co.,Ltd.
Category: otc | Type: HUMAN OTC DRUG LABEL
Date: 20250304

ACTIVE INGREDIENTS: MINOXIDIL 5 g/100 mL; CAFFEINE 0.2 g/100 mL; BIOTIN 0.3 g/100 mL; NIACINAMIDE 0.2 g/100 mL
INACTIVE INGREDIENTS: WATER; ALCOHOL; PROPYLENE GLYCOL

5%Minoxidil Hair Growth Serum

ACTIVE INGREDIENT

Minoxidil 5%
Biotin 0.3%
Niacinamide 0.2%
Caffeine 0.2%

PURPOSE

Hair regrowth treatment

INDICATIONS AND USAGE

Use: To regrow hair of scalp and beard

WARNINGS

For extemal use only.

Avoid contactwith eyes. lf contact occurs, rinse thoroughlywith water.

Do not use: On broken or irritated scalp

WHEN USING

When Using Section: When using this productavoid contact with eyes. lf contact occurs.rinse thoroughly with water.

Discontinue use if any irritation or adversereaction occurs.

Keep out of reach of Children.

DOSAGE AND ADMINISTRATION

Directions: Apply twice daily (morning andnight) as a man and once as a woman. Afterapplication, proceed with an active scalpmassage for 3-5 minutes until the product isfully absorbed.

INACTIVE INGREDIENT

Water
Alcohol
Propylene Glycol